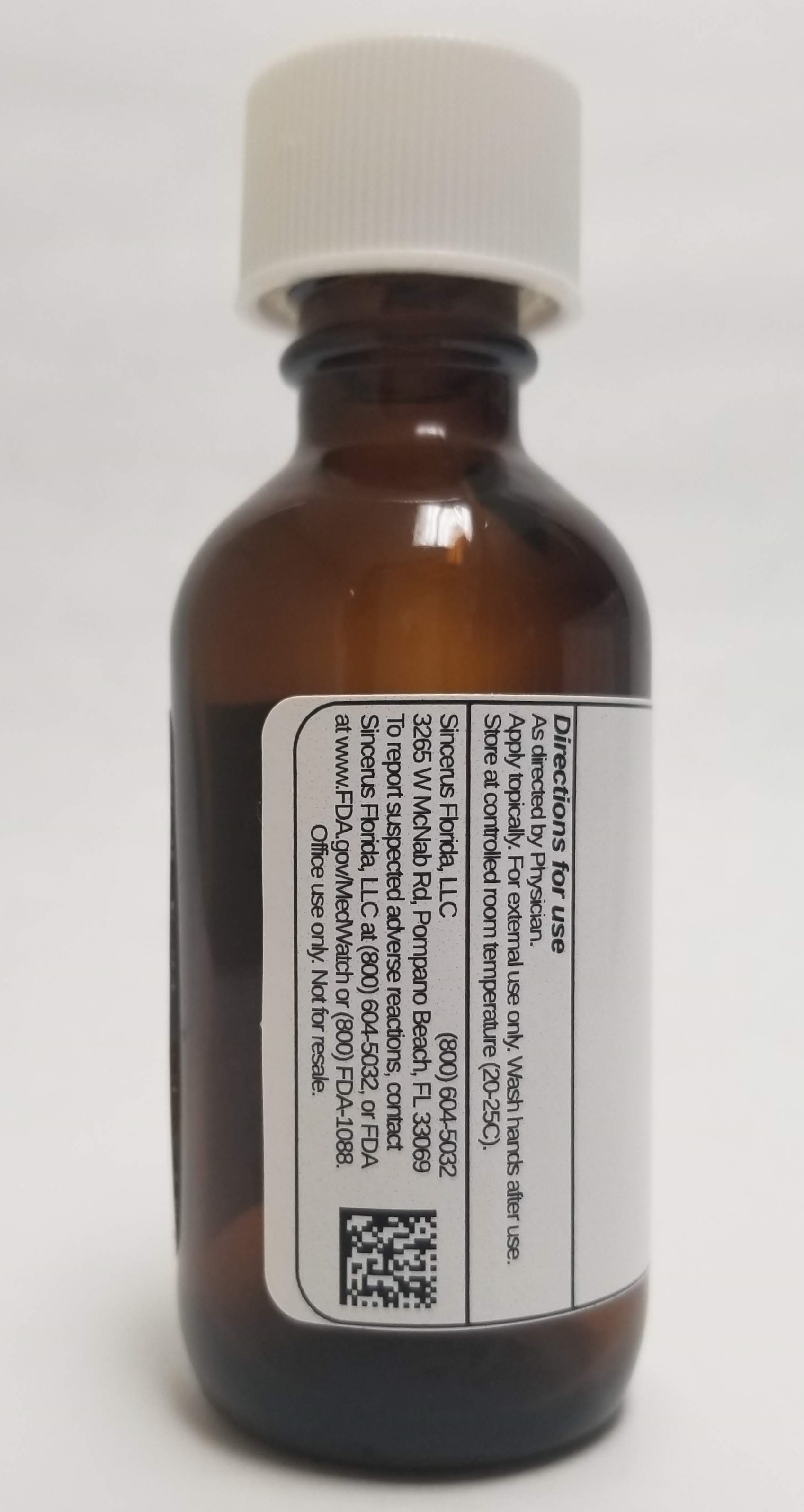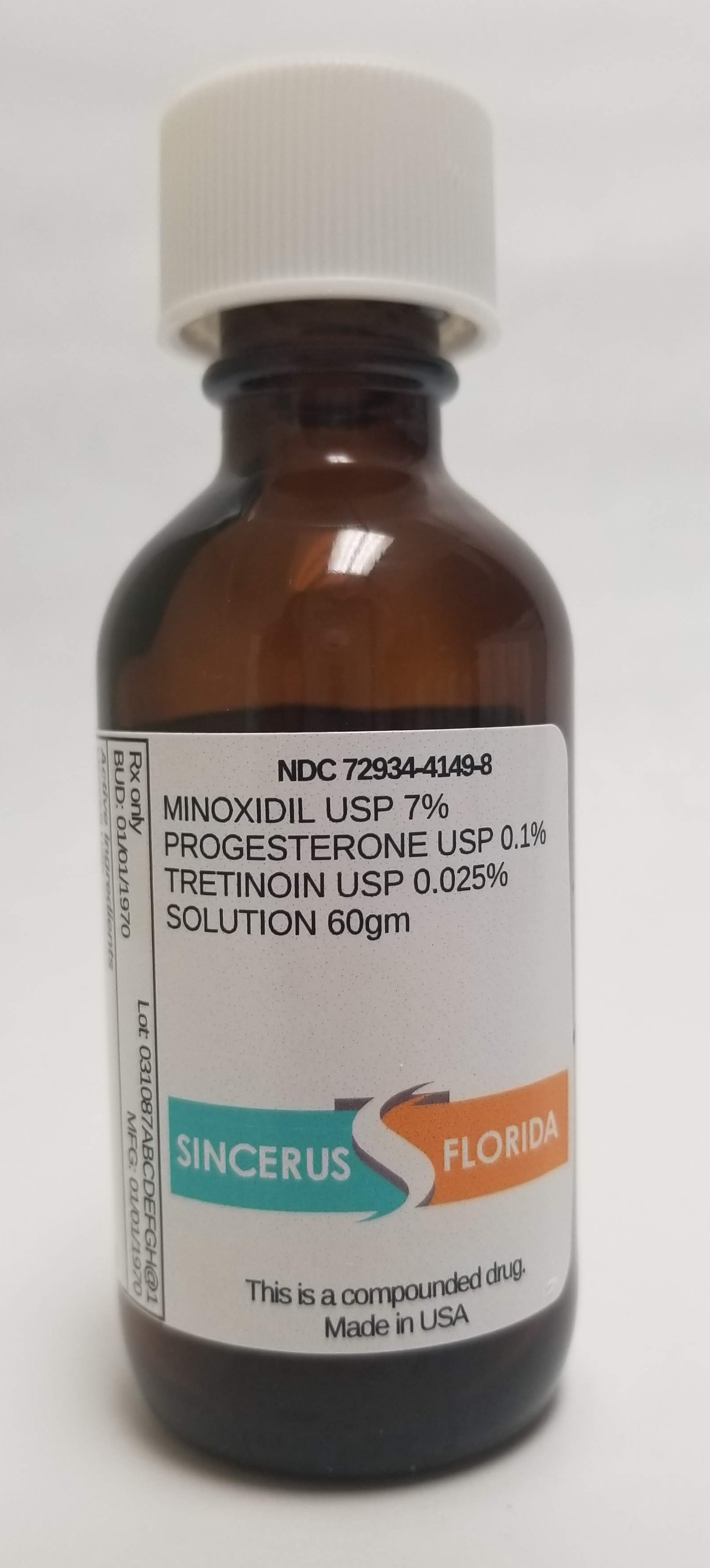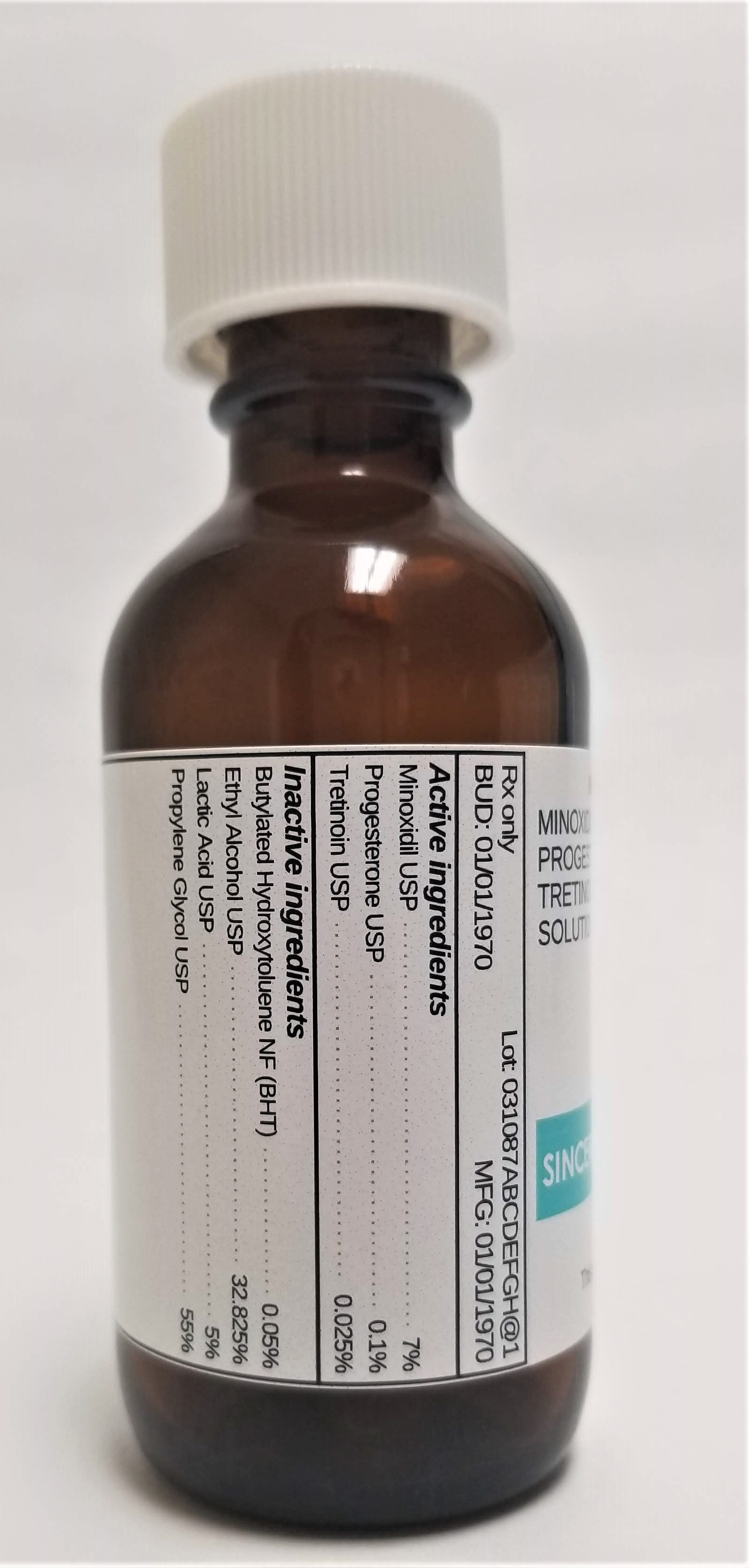 DRUG LABEL: MINOXIDIL 7% / PROGESTERONE 0.1% / TRETINOIN 0.025%
NDC: 72934-4149 | Form: SOLUTION
Manufacturer: Sincerus Florida, LLC
Category: prescription | Type: HUMAN PRESCRIPTION DRUG LABEL
Date: 20190506

ACTIVE INGREDIENTS: PROGESTERONE 0.1 g/100 g; MINOXIDIL 7 g/100 g; TRETINOIN 0.025 g/100 g

MINOXIDIL 7% / PROGESTERONE 0.1% / TRETINOIN 0.025%